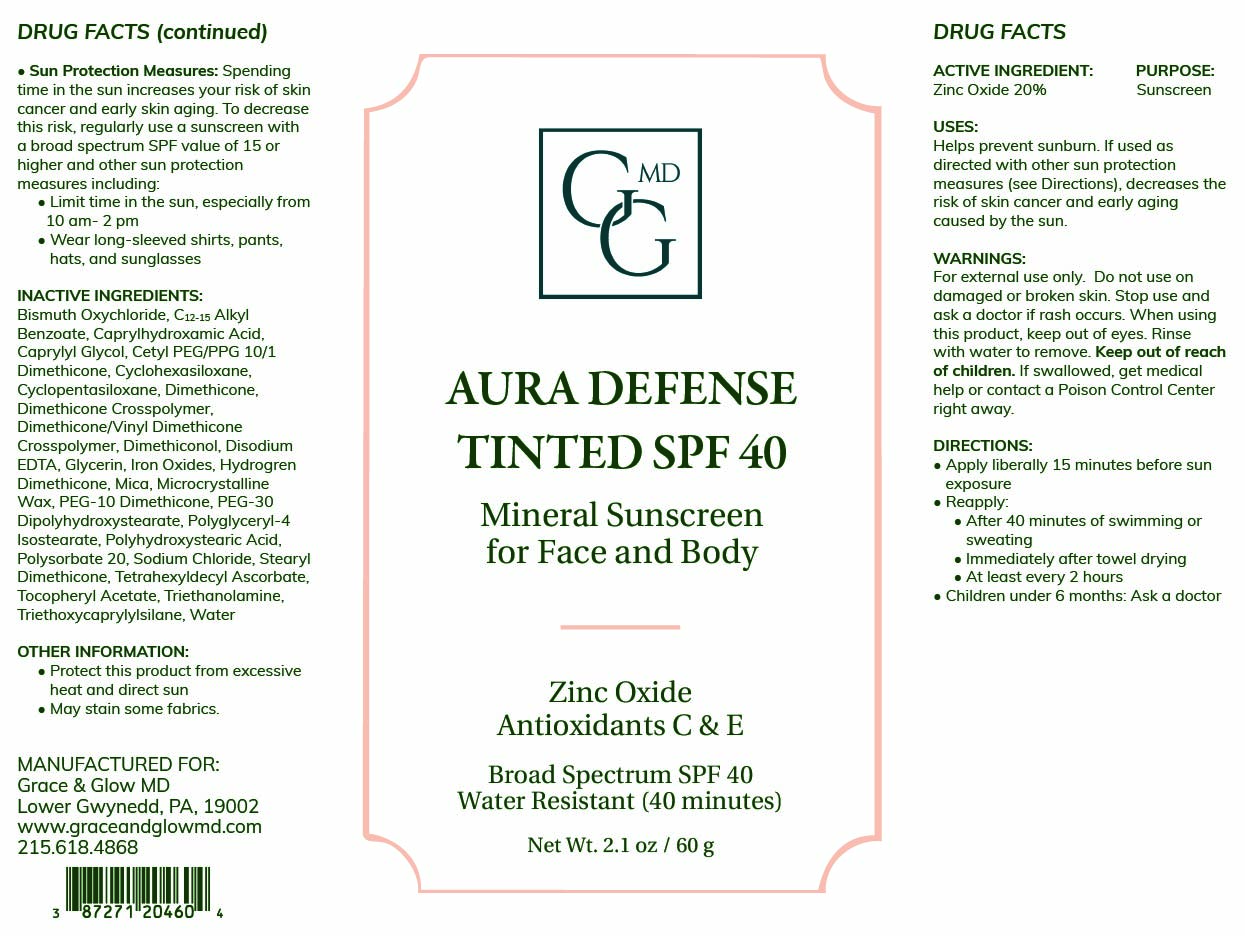 DRUG LABEL: Aura Defense
NDC: 87271-204 | Form: CREAM
Manufacturer: Grace and Glow MD LLC
Category: otc | Type: HUMAN OTC DRUG LABEL
Date: 20260225

ACTIVE INGREDIENTS: ZINC OXIDE 200 mg/1 g
INACTIVE INGREDIENTS: C12-15 ALKYL BENZOATE; DIMETHICONE; TRIETHANOLAMINE; MICROCRYSTALLINE WAX; CAPRYLYL GLYCOL; CAPRYLHYDROXAMIC ACID; EDETATE DISODIUM ANHYDROUS; GLYCERIN; PEG-10 DIMETHICONE (600 CST); SODIUM CHLORIDE; CYCLOPENTASILOXANE; HYDROGEN DIMETHICONE (20 CST); DIMETHICONOL (2000 CST); POLYGLYCERYL-4 ISOSTEARATE; STEARYL DIMETHICONE (400 MPA.S AT 50C); WATER; CETYL PEG/PPG-10/1 DIMETHICONE (HLB 4); DIMETHICONE CROSSPOLYMER; PEG-30 DIPOLYHYDROXYSTEARATE; POLYHYDROXYSTEARIC ACID (2300 MW); TETRAHEXYLDECYL ASCORBATE; MICA; ALPHA-TOCOPHEROL ACETATE; CYCLOHEXASILOXANE; POLYSORBATE 20; CI 77491; CI 77499; DIMETHICONE/VINYL DIMETHICONE CROSSPOLYMER (SOFT PARTICLE); BISMUTH OXYCHLORIDE; CI 77492; TRIETHOXYCAPRYLYLSILANE

ACTIVE INGREDIENT

Zinc Oxide 20%

PURPOSE

Sunscreen

INDICATIONS AND USAGE

Helps Prevent Sunburn. If used as directed with other sun protection measures (see “Directions”), decreases the risk of skin cancer and early skin aging caused by the sun.

WARNINGS

For external use only. Do not use on broken or damaged skin. Stop use and ask a doctor if rash occurs. When using this product, keep out of eyes. Rinse with water to remove. Keep out of reach of children. If swallowed, get medical help or contact a poison control center right away.

Keep out of reach of children

DOSAGE AND ADMINISTRATION

Apply liberally 15 minutes before sun exposure. Use a water-resistant product if swimming or sweating. Reapply at least every 2 hours. Children under 6 months: Ask a doctor. Sun Protection Measures: Spending time in the sun increases your risk of skin cancer and early skin aging. To decrease this risk, regularly use a sunscreen with a Broad-Spectrum SPF value of 15 or higher and other sun protection measures including: Limit time in the sun, especially from 10 a.m. - 2 p.m. Wear long-sleeved shirts, pants, hats and sunglasses.

INACTIVE INGREDIENT

Bismuth Oxychloride, C12-15 Alkyl Benzoate, Caprylhydroxamic Acid, Caprylyl Glycol, Cetyl PEG/PPG-10/1 Dimethicone, Cyclohexasiloxane, Cyclopentasiloxane, Dimethicone, Dimethicone Crosspolymer, Dimethicone/Vinyl Dimethicone Crosspolymer, Dimethiconol, Disodium EDTA, Glycerin, Hydrogen Dimethicone, Iron Oxides, Mica, Microcrystalline Wax, PEG-10 Dimethicone, PEG-30 Dipolyhydroxystearate, Polyglyceryl-4 Isostearate, Polyhydroxystearic Acid, Polysorbate 20, Sodium Chloride, Stearyl Dimethicone, Tetrahexyldecyl Ascorbate, Tocopheryl Acetate, Triethanolamine, Triethoxycaprylylsilane, Water

OTHER SAFETY INFORMATION

- Protect this product from excessive heat and direct sun
- May stain some fabrics